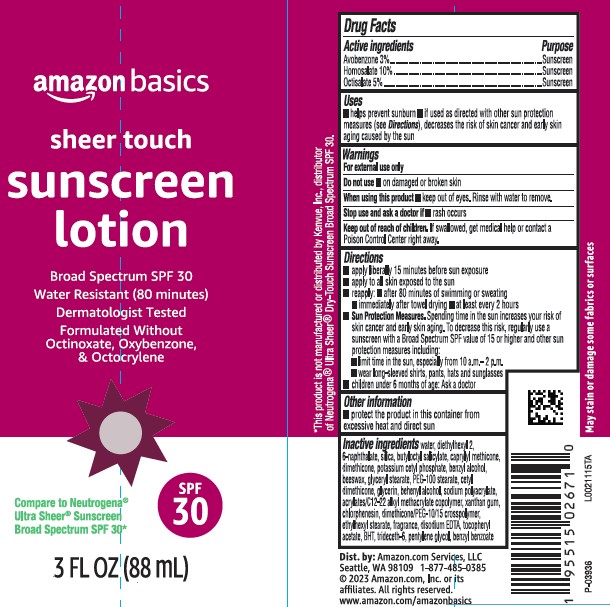 DRUG LABEL: Sheer Touch Sunscreen SPF 30
NDC: 72288-932 | Form: LOTION
Manufacturer: Amazon.com Services LLC
Category: otc | Type: HUMAN OTC DRUG LABEL
Date: 20250818

ACTIVE INGREDIENTS: OCTISALATE 50 mg/1 mL; AVOBENZONE 30 mg/1 mL; HOMOSALATE 100 mg/1 mL
INACTIVE INGREDIENTS: WATER; DIETHYLHEXYL 2,6-NAPHTHALATE; SILICON DIOXIDE; BUTYLOCTYL SALICYLATE; CAPRYLYL TRISILOXANE; DIMETHICONE; POTASSIUM CETYL PHOSPHATE; BENZYL ALCOHOL; YELLOW WAX; GLYCERYL MONOSTEARATE; PEG-100 STEARATE; CETYL DIMETHICONE 150; GLYCERIN; DOCOSANOL; SODIUM POLYACRYLATE (8000 MW); BUTYL ACRYLATE/C16-C20 ALKYL METHACRYLATE/METHACRYLIC ACID/METHYL METHACRYLATE COPOLYMER; XANTHAN GUM; CHLORPHENESIN; DIMETHICONE/PEG-10/15 CROSSPOLYMER; ETHYLHEXYL STEARATE; EDETATE DISODIUM ANHYDROUS; .ALPHA.-TOCOPHEROL ACETATE; BUTYLATED HYDROXYTOLUENE; TRIDECETH-6; PENTYLENE GLYCOL; BENZYL BENZOATE

Basics D32.000/D32AA
Sheer Touch Sunscreen SPF 30

Active Ingredients

Avobenzone 3%

Homosalate 10%

Octisalate 5%

Purpose

Sunscreen

Uses

- helps prevent sunburn
- if used as directed with other sun protection measures (See Directions), decreases the risk of skin cancer and early skin aging caused by the sun

Warnings

For external use only

Do not use

- on damaged or broken skin

When using this product

- keep out of eyes. Rinse with water to remove.

Stop use and ask a doctor if

- rash occurs

Keep out of reach of children.

If swallowed, get medical help or contact a Poison Control right away.

Directions

- apply liberaly 15 minutes before sun exposure
- apply to all skin exposed to the sun
- reapply:
- after 80 minutes of swimming or sweating
- immediately after towel drying
- at least every 2 hours
- Sun Protection Measures. Spending time in the sun increases your risk of skin cancer and early skin aging. To decrease this risk, regularly use a sunscreen with Broad Spectrum SPF value of 15 or higher and other sun protection measures including:
- limit time in the sun, especialy from 10 a.m.-2 p.m.
- wear long-sleeved shirts, pants, hats and sunglasses
- children under 6 months of age: Ask a doctor

Other information

- protect the product in this container from excessive heat and direct sun

Inactive ingredients

water, diethylhexyl 2, 6-naphthalate, silica, butyloctyl salicylate, caprylyl methicone, dimethicone, potassium cetyl phosphate, benzyl alcohol, beeswax, glyceryl stearate, PEG-100 stearate, cetyl dimethicone, glycerin, behenyl alcohol, sodium polyacrylate, acrylates/C12-22 alkyl methacrylate copolymer, xanthan gum, chlorphenesin, dimethicone/PEG-10/15 crosspolymer, ethylhexyl stearate, fragrance, disodium EDTA, tocopheryl acetate, BHT, trideceth-6, pentylene glycol, benzyl benzoate

Disclaimer

*This product is not manufactured or distributed by Kenvue, Inc., distributor of NeutrogenaUltra Sheer Dry-Touch Sunscreen Broad Spectrum SPF 30.

May stain or damage some fabrics or surfaces.

Adverse Reactions

Dist. by: Amazon.com Services, LLC

Seattle, WA 98109 1-877-485-0385

© 2023 Amazon.com, Inc. or its affiliates. All rights reserved.

www.amazon.com/amazonbasics

Principal display panel

amazon basics

sheer touch

sunscreen lotion

Broad Spectrum SPF 30

Water Resistant (80 minutes)

Dermatologists Tested

Formulated without Octinoxate, Oxybenzone, & Octocrylene

Compare to Nautrogena®Ultra Sheer Sunscreen Broad Spectrum SPF 30*

SPF 30

3 FL OZ (88 mL)